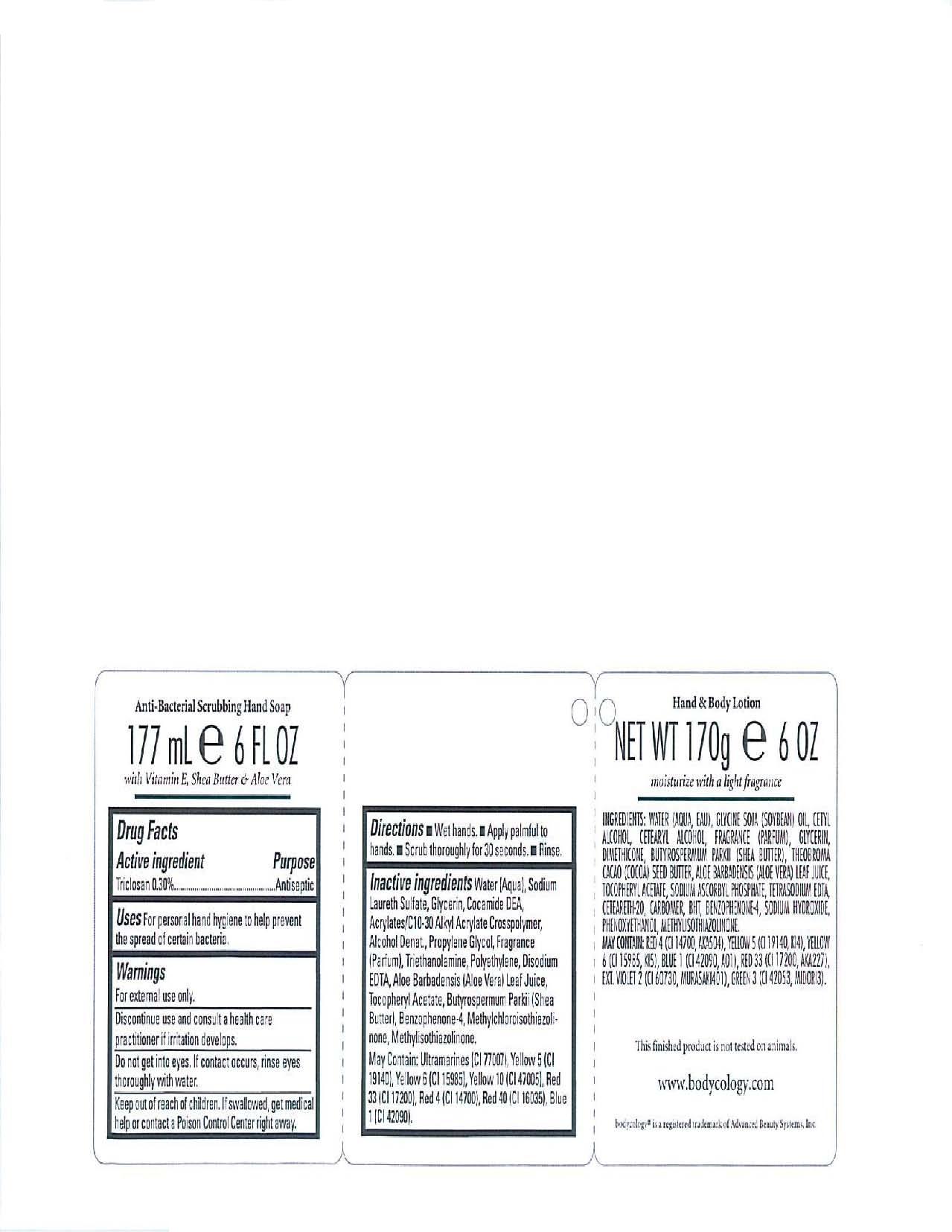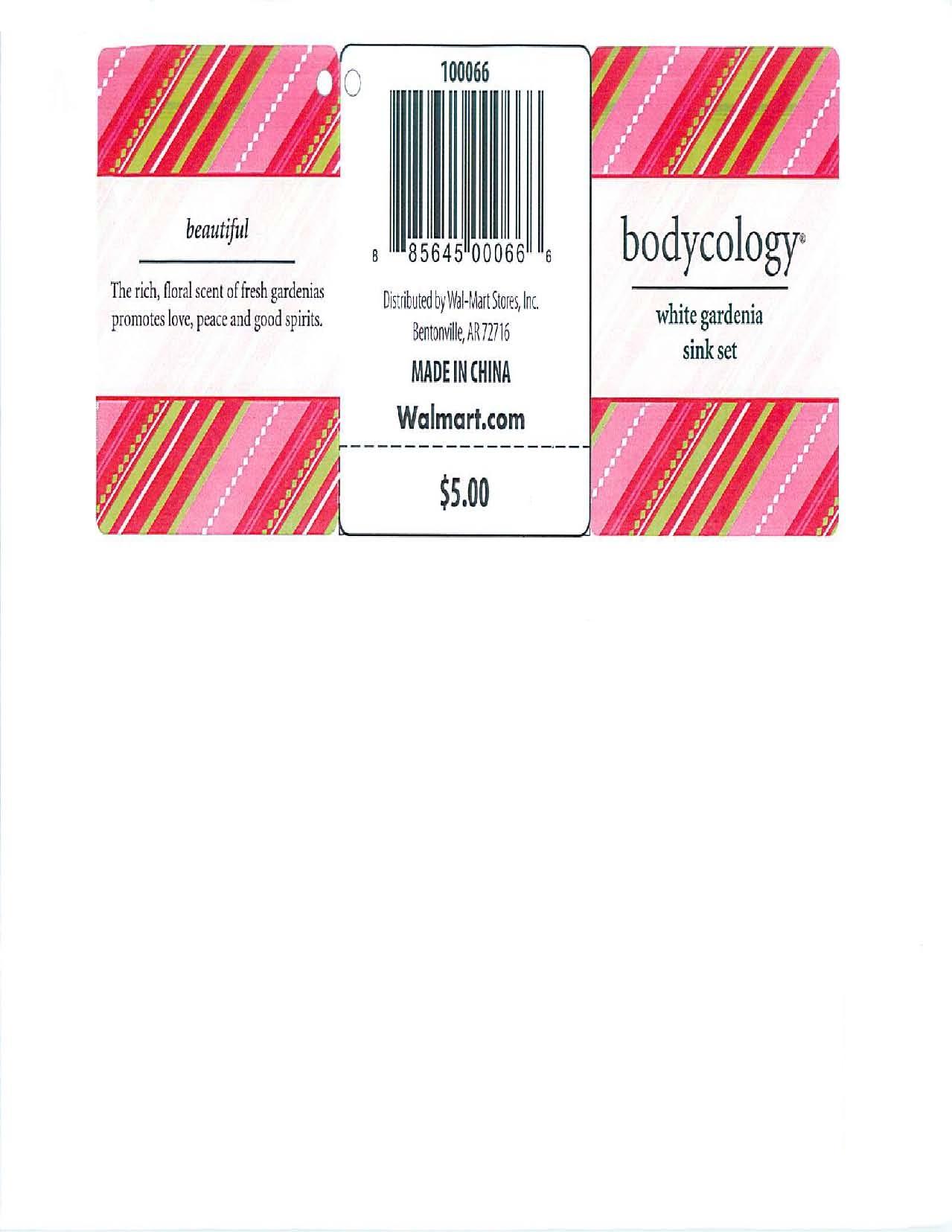 DRUG LABEL: Bodycology
NDC: 51706-115 | Form: GEL
Manufacturer: Landy International
Category: otc | Type: HUMAN OTC DRUG LABEL
Date: 20100629

ACTIVE INGREDIENTS: TRICLOSAN 0.30 mL/100 mL

White Gardenia

Active Ingredients Purpose

Triclosan 0.30% Antiseptic

Warnings:

-For external use only.

-Discontinue use and consult a health care practitioner if irritation develops

-Do not get into eyes. If contact occurs, rinse eyes thoroughly with water.

-Keep out of reach of children. If swallowed, get medical help of contact a Poison Control Center right away

INDICATIONS AND USAGE

Uses: For personal hand hygiene to help prevent the spread of certain bacteria

Directions: Wet hands, apply palm to hands, scrub thoroughly for 30 seconds, rinse

INACTIVE INGREDIENT

Inactive Ingredients: Water (Aqua), Sodium Laureth Sulfate, Glycerin, Cocamide DEA, Acrylates/C10-30 Alkyl Acrylate Crosspolymer, Alcohol Denat., Propylene Glycol, Fragrance (Parfum), Triethanolamine, Polyethylene, Disodium EDTA, Aloe Barbadensis (Aloe Vera) Leaf Juice, Tocopheryl Acetate, Butyrospermum, Parkii (Shea Butter), Benzophenone-4, Methylchloroisothiazolinone, Methylisothiazolinone. May Contain: Ultramarines (CI 77007), Yellow 5 (CI 19140), Yellow 6 (CI 15985), Yellow 10 (CI 47005), Red 33 (CI 17200), Red 4 (CI 14700), Red 40 (CI 16035), Blue 1 (CI 42090)

PACKAGE LABEL

Bodycology

White Gardenia Sink Set

Anti-Bacterial Scrubbing Hand Soap

177 mL/ 6 fl.oz.

Hand and Body Lotion

170g / 6oz.